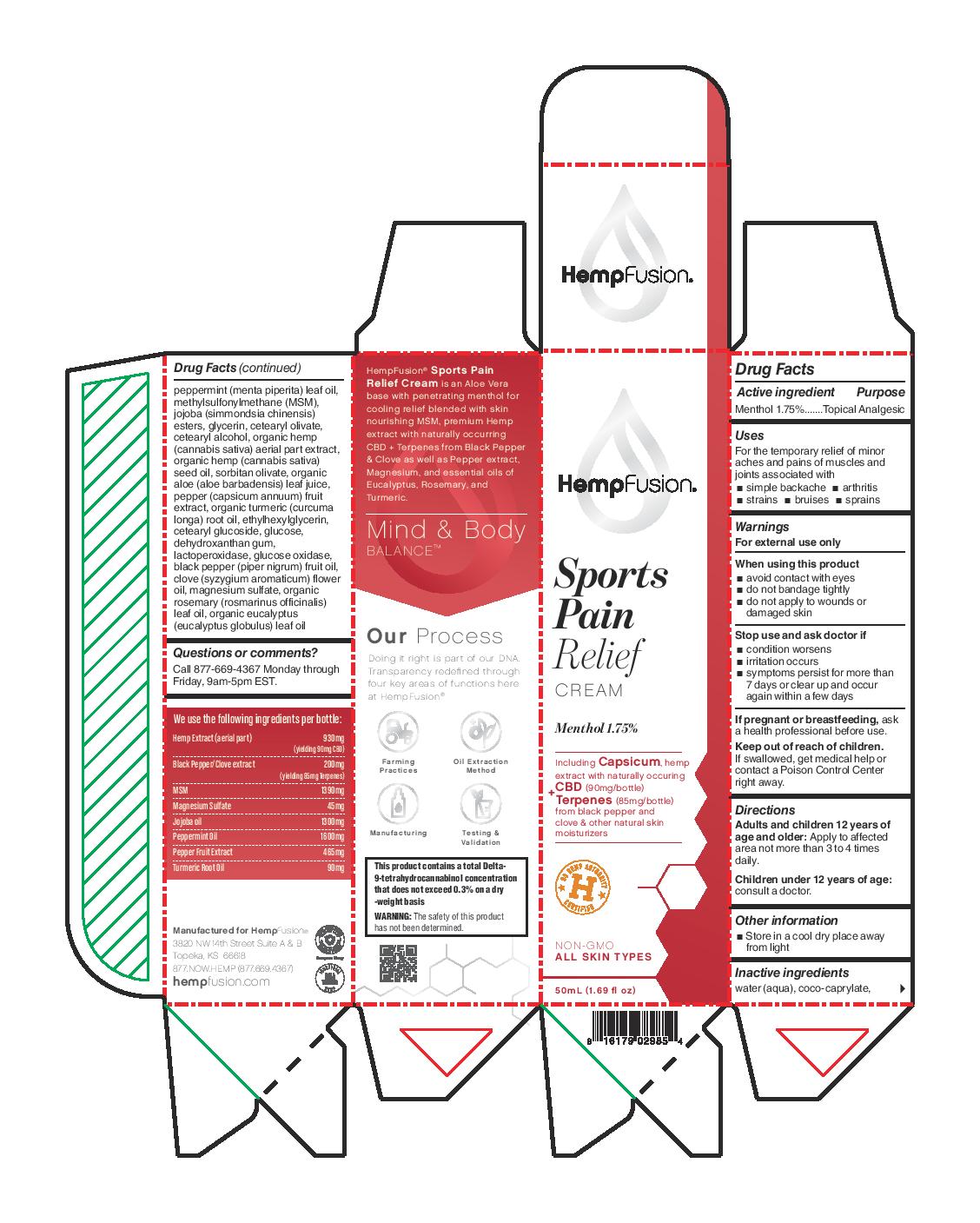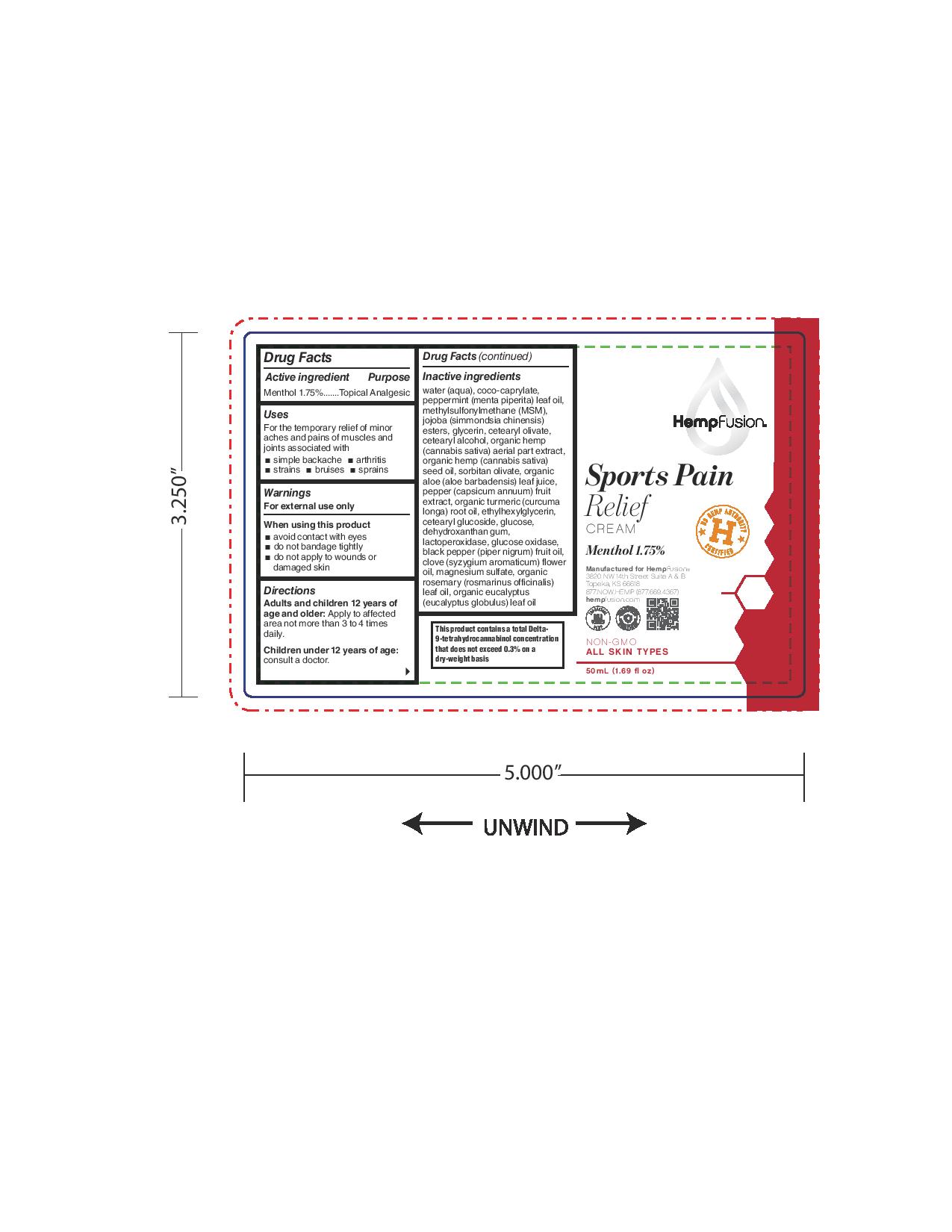 DRUG LABEL: Sports Pain Relief Cream
NDC: 73672-985 | Form: CREAM
Manufacturer: HEMPFUSION, INC.
Category: otc | Type: HUMAN OTC DRUG LABEL
Date: 20210317

ACTIVE INGREDIENTS: MENTHOL 17.5 mg/1 mL
INACTIVE INGREDIENTS: ALOE; CETEARYL GLUCOSIDE; BLACK PEPPER OIL; EUCALYPTUS OIL; PEPPERMINT OIL; DIMETHYL SULFONE; CETOSTEARYL ALCOHOL; CANNABIS SATIVA SEED OIL; SORBITAN OLIVATE; WATER; COCO-CAPRYLATE; HYDROLYZED JOJOBA ESTERS (ACID FORM); GLYCERIN; CETEARYL OLIVATE; HEMP; PAPRIKA; TURMERIC OIL; ETHYLHEXYLGLYCERIN; ANHYDROUS DEXTROSE; DEHYDROXANTHAN GUM; MYELOPEROXIDASE; GLUCOSE OXIDASE; CLOVE OIL; MAGNESIUM SULFATE, UNSPECIFIED FORM; ROSEMARY OIL

Sports Pain Relief Cream

Active ingredient

Menthol 1.75%

Purpose

Menthol 1.75%.......Topical Analgesic

Uses

For the temporary relief of minor aches and pains of muslces and joints associated with

- simple backache
- arthritis
- strains
- bruises
- sprains

Warnings

For external use only

When using this product

- avoid contact with eyes
- do not bandage tightly
- do not apply to wounds or damaged skin

Stop use and ask doctor if

- condition worsens
- irritation occurs
- symptoms persist for more than 7 days or clear up and occur again within a few days

PREGNANCY OR BREAST FEEDING

If pregnant or breastfeeding, ask a health professional before use.

Keep out of reach of children. If swallowed, get medical help or contact a Poison Control Center right away.

Directions

Adults and children 12 years of age and older. Apply to affected area not more than 3 to 4 times daily.

Children under 12 years of age: consult a doctor.

Other information

- Store in a cool dry place away from light

Inactive ingredients

water (aqua), coco-caprylate, peppermint (menta piperita) leaf oil, methylsulfonylmethane (MSM), jojoba (simmondsia chinensis)

esters, glycerin, cetearyl olivate, cetearyl alcohol, organic hemp (cannabis sativa) aerial part extract, organic hemp (cannabis sativa) seed oil, sorbitan olivate, organic aloe (aloe barbadensis) leaf juice, pepper (capsicum annuum) fruit extract, organic turmeric (curcuma longa) root oil, ethylhexylglycerin, cetearyl glucoside, glucose, dehydroxanthan gum, lactoperoxidase, glucose oxidase, black pepper (piper nigrum) fruit oil,clove (syzygium aromaticum) flower oil, magnesium sulfate, organic rosemary (rosmarinus officinalis) leaf oil, organic eucalyptus (eucalyptus globulus) leaf oil

Questions or comments?

Call 877-669-4367 Monday through Friday, 9am-5pm EST.

Principal Display Panel

HempFusion

Sports

Pain

Relief

CREAM

Menthol 1.75%

Including Capsicum, hemp extract with naturally occuring CBD (90mg/bottle) + Terpenes (85mg/bottle) from black pepper and clove & other natural skin moisturizers.

U.S. HEMP AUTHORITY H CERTIFIED

NON-GMO

ALL SKIN TYPES

50mL (1.69 fl oz)